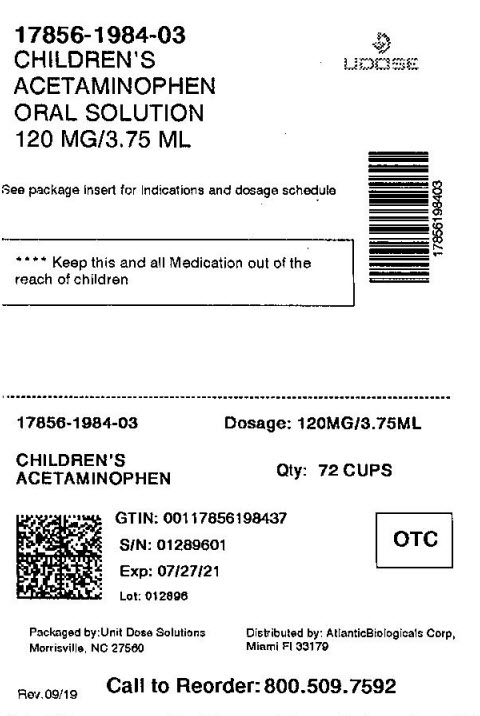 DRUG LABEL: Childrens MAPAP Acetaminophen
NDC: 17856-1984 | Form: LIQUID
Manufacturer: ATLANTIC BIOLOGICALS CORP.
Category: otc | Type: HUMAN OTC DRUG LABEL
Date: 20210128

ACTIVE INGREDIENTS: Acetaminophen 160 mg/5 mL
INACTIVE INGREDIENTS: Glycerin; Sorbitol; Sodium Benzoate; Anhydrous citric acid; FD&C Red no. 40; Water; SACCHARIN SODIUM; Propylene glycol; PRUNUS SEROTINA BARK; POLYETHYLENE GLYCOL 1450; D&C RED NO. 33

Childrens MĀPAP Acetaminophen Liquid®

Active ingredient (in each TSP (5 mL))

Acetaminophen 160 mg

Purpose

Fever reducer-Pain reliever

Uses

Temporarily relieves minor aches and pains due to:

- the common cold
- flu
- headache
- sore throat
- toothache

Temporarily reduces fever

Warnings

Liver warning

This product contains acetaminophen. Severe liver damage may occur if your child takes:

- more than 5 doses in 24 hours, which is the maximum daily amount
- with other drugs containing acetaminophen

Sore throat warning

If sore throat is severe, persists for more than 2 days, is accompanied or followed by fever, headache, rash, nausea, or vomiting, consult a doctor promptly.

Do not use

- with any other product containing acetaminophen (prescription or nonprescription). If you are not sure whether a drug contains acetaminophen, ask a doctor or pharmacist

ASK DOCTOR

liver disease Ask a doctor before use if your child has

ASK DOCTOR/PHARMACIST

taking the blood thinning drug warfarin. Ask a doctor or pharmacist before use if your child is

Stop use and ask a doctor if

- pain gets worse or last for more than 5 days
- fever gets worse or last for more than 3 days
- new symptoms occur
- redness or swelling is present

These could be signs of a serious condition.

PREGNANCY OR BREAST FEEDING

ask a health professional before use If pregnant or breast-feeding,

Keep out of the reach of children.

Overdose warning

Taking more than the recommended dose (overdose) may cause liver damage. In case of overdose, get medical help or contact a Poison Control Center (1-800-222-1222) right away. Quick medical attention is critical for adults as well as children even if you do not notice any signs or symptoms.

Directions

- this product does not contain directions or complete warnings for adult use
- find right dose on chart
- if possible, use weight to dose; otherwise, use age
- if needed, repeat dose every 4 hours
- do not use more than 5 doses in 24 hours

Weight | Age | Dose
under 24 lbs | Under 2 years | ask a doctor
24 to 35 lbs | 2 to 3 years | 1 TSP (5 mL)
36 to 47 lbs | 4 to 5 years | 1 1/2 TSP (7.5 mL)
48 to 59 lbs | 6 to 8 years | 2 TSP (10 mL)
60 to 71 lbs | 9 to 10 years | 2 1/2 TSP (12.5 mL)
72 to 95 lbs | 11 years | 3 TSP (15 mL)

Other information

- sodium 1mg Each TSP(5 mL) contains:
- TAMPER-EVIDENT: Do not use this product if inner foil seal over mouth of the bottle is cut, torn, broken, or missing.
- store at 20° - 25°C (68° – 77°F)
- this product is not the same concentration as Infants' Drops. For accurate dosing, follow the dosing instructions on this label.

Inactive ingredients

artificial flavor, citric acid anhydrous, D&C Red #33, FD&C Red #40, glycerin, polyethylene glycol 1450, propylene glycol, purified water, sodium benzoate, sodium saccharin,sorbitol

Questions?

To Report Adverse Drug Event call 1-800-616-2471 Weekdays, 9AM - 5PM Eastern Time